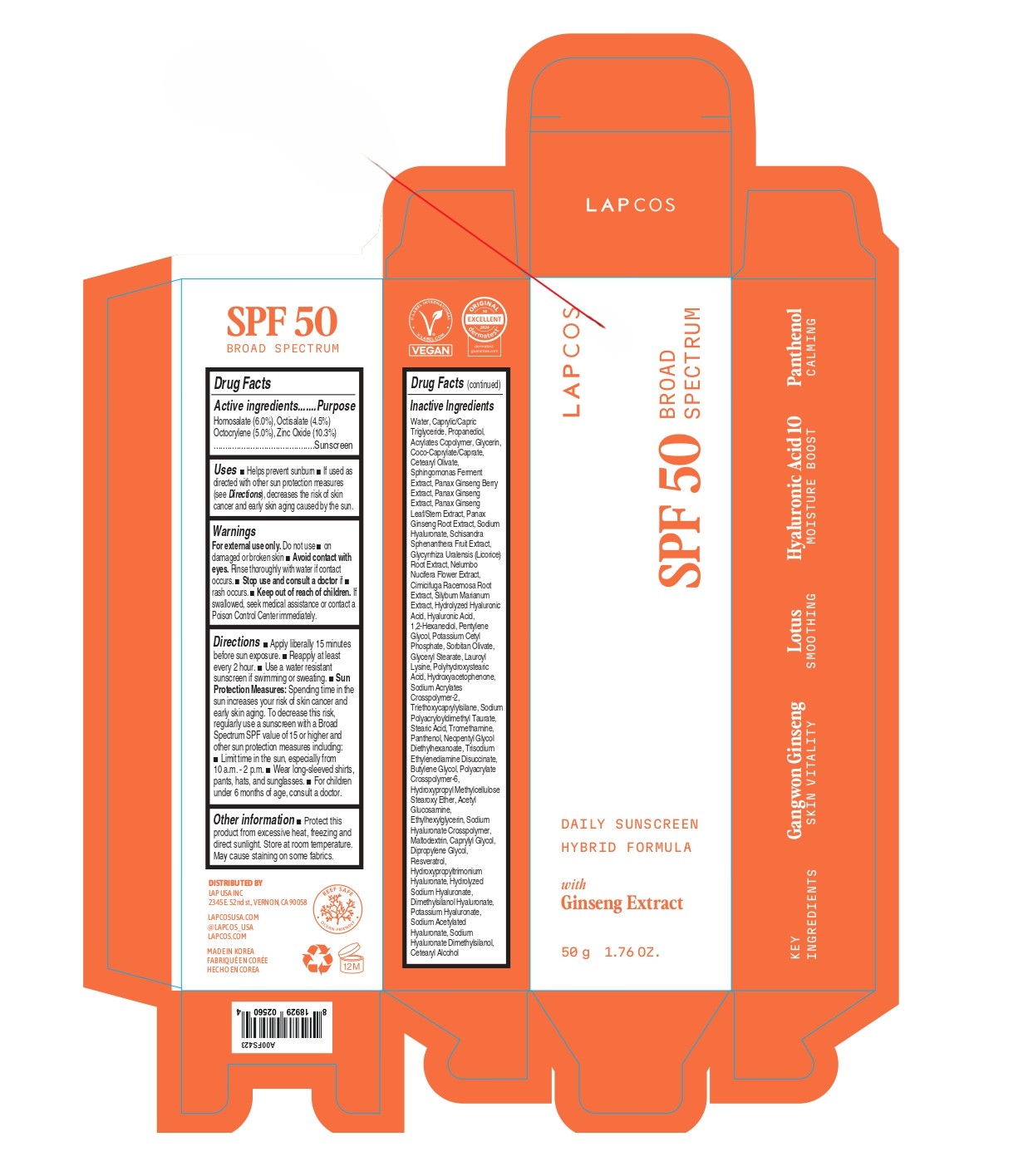 DRUG LABEL: LAPCOS DAILY SUNSCREEN SPF 50
NDC: 85586-001 | Form: CREAM
Manufacturer: LAP USA, INC.
Category: otc | Type: HUMAN OTC DRUG LABEL
Date: 20250501

ACTIVE INGREDIENTS: ETHYLHEXYL SALICYLATE 4.5 g/100 g; OCTOCRYLENE 5 g/100 g; HOMOSALATE 6 g/100 g; ZINC OXIDE 10.3 g/100 g
INACTIVE INGREDIENTS: LAUROYL LYSINE; HYALURONIC ACID; CAPRYLIC/CAPRIC TRIGLYCERIDE; PANAX GINSENG WHOLE; RESVERATROL; PROPANEDIOL; ETHYLHEXYLGLYCERIN; DIMETHYLSILANOL HYALURONATE; POTASSIUM CETYL PHOSPHATE; BUTYL ACRYLATE/METHYL METHACRYLATE/METHACRYLIC ACID COPOLYMER (18000 MW); PANAX GINSENG FRUIT; PANAX GINSENG LEAF; SODIUM HYALURONATE; SILYBUM MARIANUM WHOLE; PENTYLENE GLYCOL; SODIUM ACRYLATES CROSSPOLYMER-2; TRIETHOXYCAPRYLYLSILANE; PANAX GINSENG ROOT; PEG-9 DIGLYCIDYL ETHER/SODIUM HYALURONATE CROSSPOLYMER; MALTODEXTRIN; GLYCYRRHIZA URALENSIS ROOT; CETEARYL OLIVATE; 1,2-HEXANEDIOL; SODIUM POLYACRYLOYLDIMETHYL TAURATE; NELUMBO NUCIFERA FLOWER; CIMICIFUGA RACEMOSA ROOT; SODIUM ACETYLATED HYALURONATE; HYDROXYACETOPHENONE; PANTHENOL; NEOPENTYL GLYCOL DIETHYLHEXANOATE; TRISODIUM ETHYLENEDIAMINE DISUCCINATE; ACETYL GLUCOSAMINE; POLYACRYLATE CROSSPOLYMER-6; SORBITAN OLIVATE; SCHISANDRA SPHENANTHERA FRUIT; GLYCERYL STEARATE; BUTYLENE GLYCOL; CAPRYLYL GLYCOL; GLYCERIN; WATER; COCO-CAPRYLATE/CAPRATE; TROMETHAMINE; DIPROPYLENE GLYCOL; STEARIC ACID; CETEARYL ALCOHOL; POLYHYDROXYSTEARIC ACID (2300 MW)

Active Ingredients Purpose
Homosalate 6.0% Sunscreen
Octisalate 4.5% Sunscreen
Octocrylene 5.0% Sunscreen
Zinc Oxide 10.3% Sunscreen

INDICATIONS AND USAGE

Helps prevent sunburn If used as directed with other sun protection measures (see Directions), decreases the risk of skin cancer and early skin aging caused by the sun.

WARNINGS

For external use only.

DO NOT USE

on damaged or broken skin

WHEN USING

Avoid contact with eyes. Rinse thoroughly with water if contact occurs.

STOP USE

rash occurs.

KEEP OUT OF REACH OF CHILDREN

If swallowed, seek medical assistance or contact a Poison Control Center immediately.

DOSAGE AND ADMINISTRATION

Apply liberally 15 minutes before sun exposure. Reapply at least every 2 hour. Use a water resistant sunscreen if swimming or sweating. Sun Protection Measures: Spending time in the sun increases your risk of skin cancer and early skin aging. To decrease this risk, regularly use a sunscreen with a Broad Spectrum SPF value of 15 or higher and other sun protection measures including: Limit time in the sun, especially from 10 a.m. - 2 p.m. Wear long-sleeved shirts, pants, hats, and sunglasses. For children under 6 months of age, consult a doctor.

STORAGE AND HANDLING

Protect this product from excessive heat, freezing and direct sunlight. Store at room temperature.
May cause staining on some fabrics.

INACTIVE INGREDIENT

Water, Caprylic/Capric Triglyceride, Propanediol, Glycerin, Coco-Caprylate/Caprate, Cetearyl Olivate, 1,2-Hexanediol, Pentylene Glycol, Potassium Cetyl Phosphate, Sorbitan Olivate, Cetearyl Alcohol, Glyceryl Stearate, Lauroyl Lysine, Hydroxyacetophenone, Sodium Acrylates Crosspolymer-2, Triethoxycaprylylsilane, Sodium Polyacryloyldimethyl Taurate, Stearic Acid, Panthenol, Tromethamine, Neopentyl Glycol Diethylhexanoate, Trisodium Ethylenediamine Disuccinate, Butylene Glycol, Polyacrylate Crosspolymer-6, Panax Ginseng Berry Extract, Panax Ginseng Extract, Panax Ginseng Leaf/Stem Extract, Panax Ginseng Root Extract, Acetyl Glucosamine, Sodium Hyaluronate, Ethylhexylglycerin, Maltodextrin, Schisandra Sphenanthera Fruit Extract, Caprylyl Glycol, Glycyrrhiza Uralensis (Licorice) Root Extract, Dipropylene Glycol, Nelumbo Nucifera Flower Extract, Cimicifuga Racemosa Root Extract, Resveratrol, Silybum Marianum Extract, Dimethylsilanol Hyaluronate, Hyaluronic Acid, Sodium Acetylated Hyaluronate, BUTYL ACRYLATE/METHYL METHACRYLATE/METHACRYLIC ACID COPOLYMER (18000 MW), PEG-9 DIGLYCIDYL ETHER/SODIUM HYALURONATE CROSSPOLYMER

Purpose

Helps prevent sunburn.
If used as directed with other sun protection measures (see Directions), decreases the risk of skin cancer and early skin aging caused by the sun.

PACKAGE LABEL

LAPCOS
SPF 50
BROAD SPECTRUM
DAILY SUNSCREEN HYBRID FORMULA
with Ginseng Extract
50 g / 1.76 OZ.